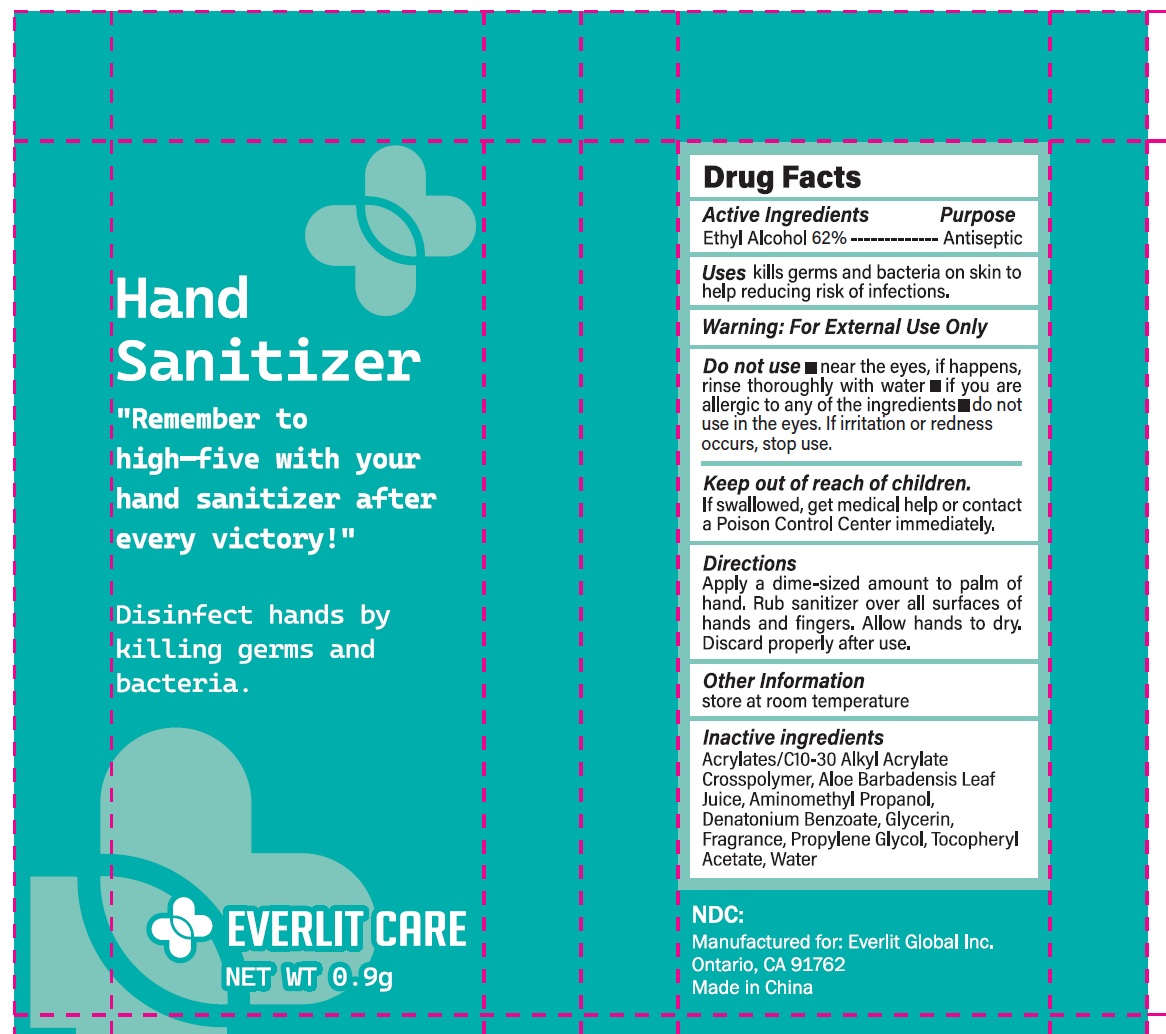 DRUG LABEL: EVERLIT CARE Hand Sanitizer
NDC: 83807-003 | Form: GEL
Manufacturer: EVERLIT GLOBAL INC.
Category: otc | Type: HUMAN OTC DRUG LABEL
Date: 20251025

ACTIVE INGREDIENTS: ALCOHOL 62 mL/100 mL
INACTIVE INGREDIENTS: WATER; GLYCERIN; PROPYLENE GLYCOL; ACRYLATES/C10-30 ALKYL ACRYLATE CROSSPOLYMER (60000 MPA.S); TOCOPHERYL GLUCOSIDE; AMINOMETHYLPROPANOL; DENATONIUM BENZOATE; ALOE ARBORESCENS LEAF JUICE

83807-003, Everlit Care Hand Sanitizer

Active ingredient

Ethyl Alcohol, 62%

Purpose Antiseptic

Uses

Kill germs and bacteria on skin to help reducing risk of infections

Warnings

For external use only.

Flammable, keep away from fire or flame.

Do not use

near the eyes, if happens, rinse thoroughly with water.

if you are allergic to any of the ingredients

Do not use in the eyes. If irritation or redness occurs, stop use.

Keep out of reach of children. If swallowed, get medical help or contact a Poison Control Center immediately.

Directions

Apply a dime sized amount to palm of hand. Rub santizer all over surfaces of hands and fingers. Allow hands to dry. Discard properly after use.

Other information

Store at room temperature

Inactive ingredients

Acrylates/ C10-C30 alkyl acrylate crossploymer, Aloe barbadensis leaf juice, Aminomethyl propanol, Denatonium benzoate, Glycerin, Propylene glycol, Fragrance, Tocopheryl acetate, Water